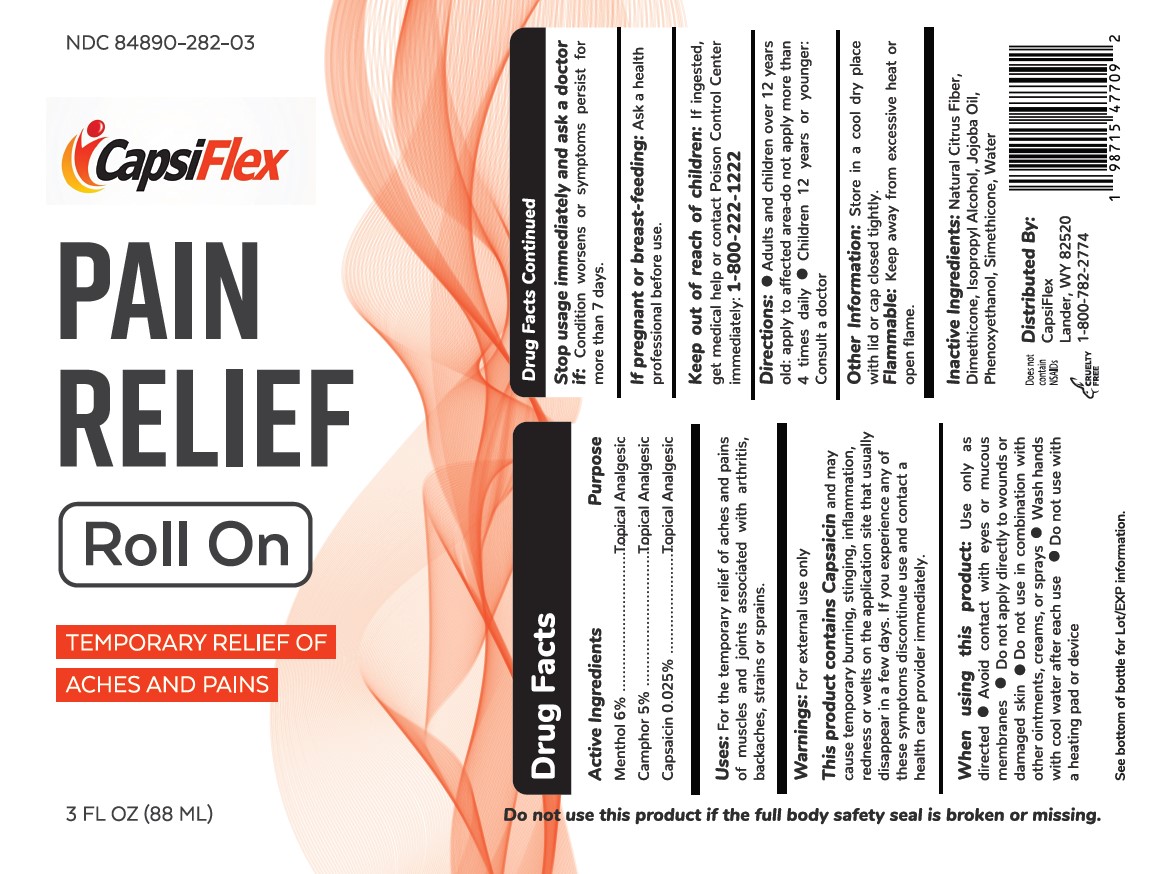 DRUG LABEL: Pain Relief Roll On
NDC: 83084-282 | Form: LIQUID
Manufacturer: Fullstack Fulfillment
Category: otc | Type: HUMAN OTC DRUG LABEL
Date: 20241223

ACTIVE INGREDIENTS: MENTHOL 0.06 g/1 g; CAMPHOR (SYNTHETIC) 0.05 g/1 g; CAPSAICIN 0.00025 g/1 g
INACTIVE INGREDIENTS: SILICON DIOXIDE; CITRUS FRUIT; PHENOXYETHANOL; JOJOBA OIL; DIMETHICONE; ISOPROPYL ALCOHOL; WATER

Active Ingredients

Menthol 6%

Camphor 5%

Capsaicin 0.025%

PURPOSE

Topical Analgesic

WARNINGS

For external Use only

WHEN USING

Use only as directed

STOP USE

Stop usage immediately and ask a doctor if condition worsens

PREGNANCY OR BREAST FEEDING

Ask a health professional before use

KEEP OUT OF REACH OF CHILDREN

if ingested get medical help

DOSAGE AND ADMINISTRATION

Adult and children over 12 years old: apply to affected area, do not appy more than 4 times daily. Children 12 years or younger consult a doctor.